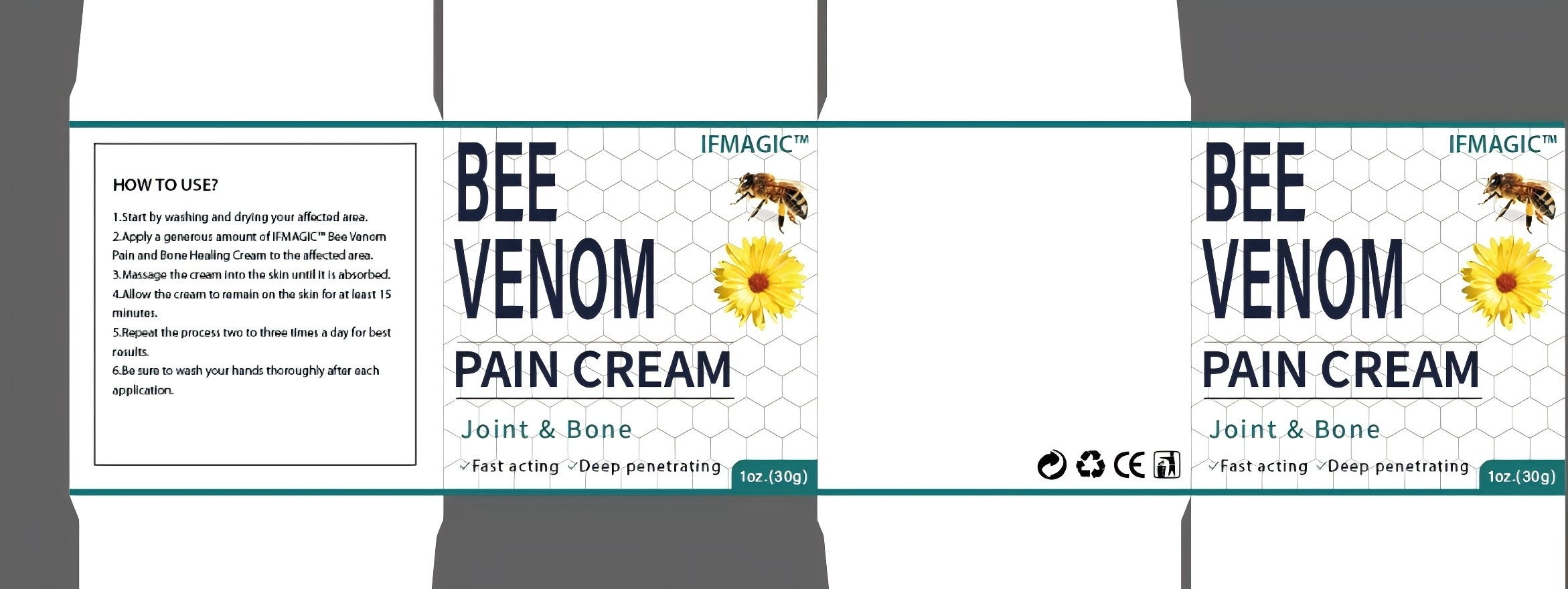 DRUG LABEL: Bee Venom Cream
NDC: 84778-019 | Form: CREAM
Manufacturer: Guangzhou Yixin Cross-border E-commerce Co., Ltd.
Category: otc | Type: HUMAN OTC DRUG LABEL
Date: 20241031

ACTIVE INGREDIENTS: ARNICA MONTANA FLOWER 10 g/10 g
INACTIVE INGREDIENTS: WATER

COMPONENTS

ArnicaFlowerExtract 10g

PURPOSE

Reduce the appearance of fine lines and wrinkles. For minor skin injuries or breakouts, bee venom cream may help speed up the healing process.

INDICATIONS AND USAGE

Reduce the appearance of fine lines and wrinkles. For minor skin injuries or breakouts, bee venom cream may help speed up the healing process.

WARNINGS

This product contains bee venom, which may cause allergic reactions. Please perform a skin test before use. If redness, stinging or other inconsistencies occur, please stop using it immediately. If you have a history of severe allergies or are sensitive to bee products, please consult a doctor before use. Pay attention to eyes and sensitive areas. If there are inconsistencies, please consult a doctor immediately. Keep out of reach of children.

DOSAGE AND ADMINISTRATION

For external use only.

DO NOT USE

Avoid contact with eyes and eyelids, as it may cause irritation or allergic reaction.
Do not apply to wounds, cuts or other skin injuries.
Avoid using on armpits, itchy areas or other sensitive areas to reduce the risk.

WHEN USING

Do not apply to wounds, cuts or other skin injuries.

STOP USE

Allergic reaction: If redness, itching, stinging, rash or other allergic symptoms occur, please stop using immediately.

Skin irritation: If you feel obvious unevenness, such as burning or pain, you should stop using it immediately.

Wounds or skin damage: If you find that your skin is weakened or infected during use, you must stop using it.

Keep out of reach of children and pets.

Do not use this box incribs,beds,carriages or play pens,This Product is not a TOY.

INACTIVE INGREDIENT

Water

SophoraFlavescensExtract

CnidiumMonnieriExtract
ArnicaFlowerExtract
RhizomaTuberExtract
Beevenomextract